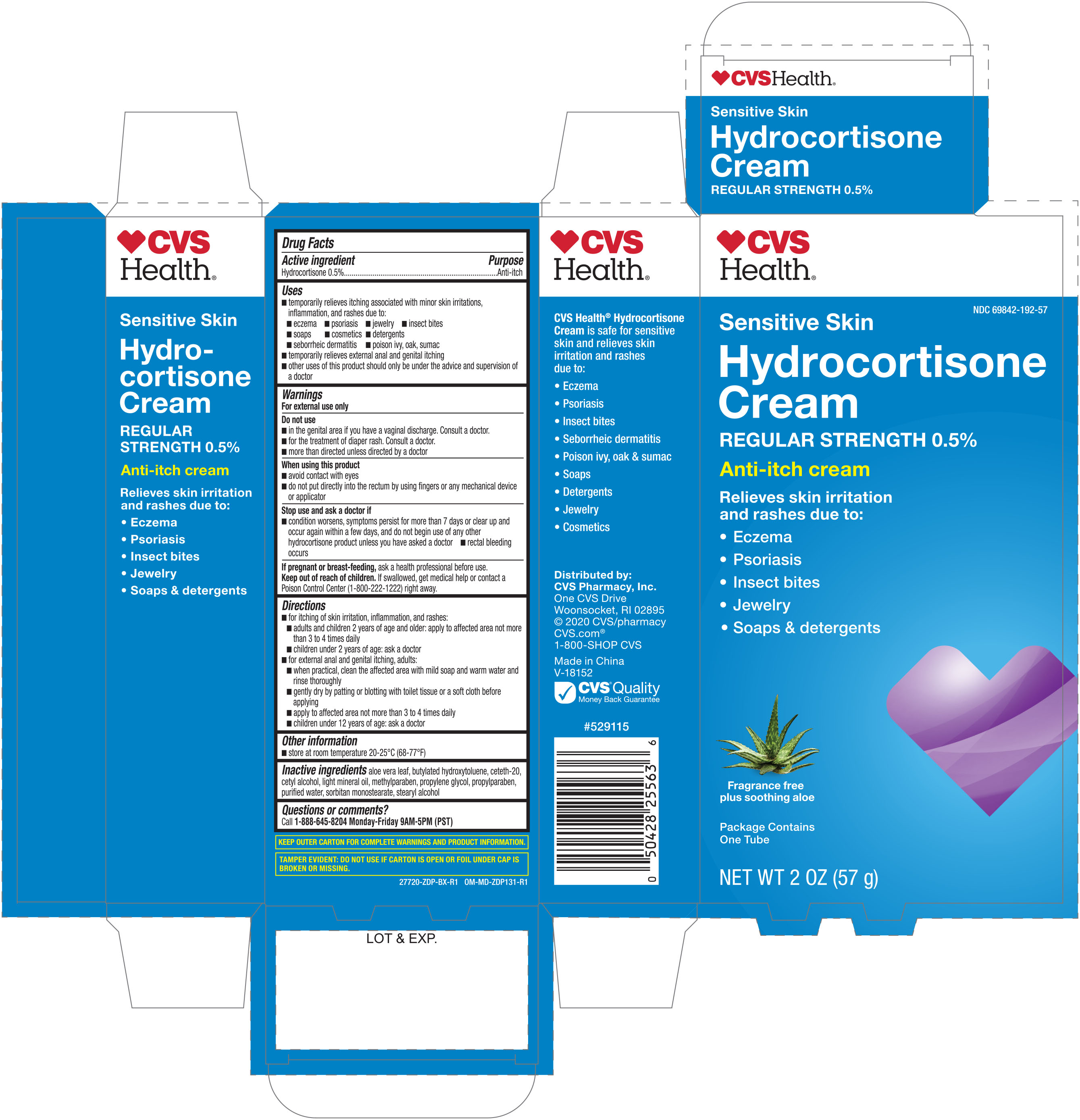 DRUG LABEL: Anti-Itch Regular Strength
NDC: 69842-192 | Form: CREAM
Manufacturer: CVS Pharmacy
Category: otc | Type: HUMAN OTC DRUG LABEL
Date: 20251030

ACTIVE INGREDIENTS: HYDROCORTISONE 5 mg/1 g
INACTIVE INGREDIENTS: PROPYLENE GLYCOL; CETETH-20; CETYL ALCOHOL; METHYLPARABEN; ALOE VERA LEAF; PROPYLPARABEN; WATER; SORBITAN MONOSTEARATE; BUTYLATED HYDROXYTOLUENE; LIGHT MINERAL OIL; STEARYL ALCOHOL

CVS Hydrocortisone Cream w/Aloe 0.5% 2oz 27720 ZDP

Active ingredient Purpose

Hydrocortisone 0.5%..................................................Anti-itch

Uses

- temporarily relieves itching associated with minor skin irritations, inflammation, and rashes due to:
- eczema
- psoriasis
- jewelry
- insect bites
- soaps
- cosmetics
- detergents
- seborrheic dermatitis
- poison ivy, oak, sumac
- temporarily relieves external anal and genital itching
- other uses of this product should only be under the advice and supervision of a doctor

Warnings

For external use only

Do not use

- in the genital area if you have a vaginal discharge. Consult a doctor.
- for the treatment of diaper rash. Consult a doctor.
- more than directed unless directed by a doctor.

When using this product

- avoid contact with eyes
- do not put directly into the rectum by using fingers or any mechanical device or applicator

Stop use and ask a doctor if

- condition worsens, symptoms persist for more than 7 days or clear up and occur again within a few days, and do not begin use of any other hydrocortisone product unless you have asked a doctor
- rectal bleeding occurs

Stop use and ask a doctor if

- condition worsens, symptoms persist for more than 7 days or clear up and occur again within a few days, and do not begin use of any other hydrocortisone product unless you have asked a doctor
- rectal bleeding occurs

PREGNANCY OR BREAST FEEDING

If pregnant or breast-feeding, ask a health professional before use.

Keep out of reach of children. If swallowed, get medical help or contact a Poison Control Center (1-800-222-1222) right away.

Directions

- for itching of skin irritation, inflammation, and rashes:
- adults and children 2 years of age and older: apply to affected area not more than 3 to 4 times daily
- children under 2 years of age: ask a doctor
- for external anal and genital itching, adults:
- when practical, clean the affected area with mild soap and warm water and rinse thoroughly
- gently dry by patting or blotting with toilet tissue or a soft cloth before applying
- apply to affected area not more than 3 to 4 times daily
- children under 12 years of age: ask a doctor

INACTIVE INGREDIENT

Inactive ingredients aloe vera leaf, butylated hydroxytoluene, ceteth-20, cetyl alcohol, light mineral oil, methylparaben, propylene glycol, propylparaben, purified water, sorbitan monostearate, stearyl alcohol

DOSAGE AND ADMINISTRATION

Distributed by:

CVS Pharmacy, Inc.

One CVS Drive

Woonsocket, RI 02895

Made in China